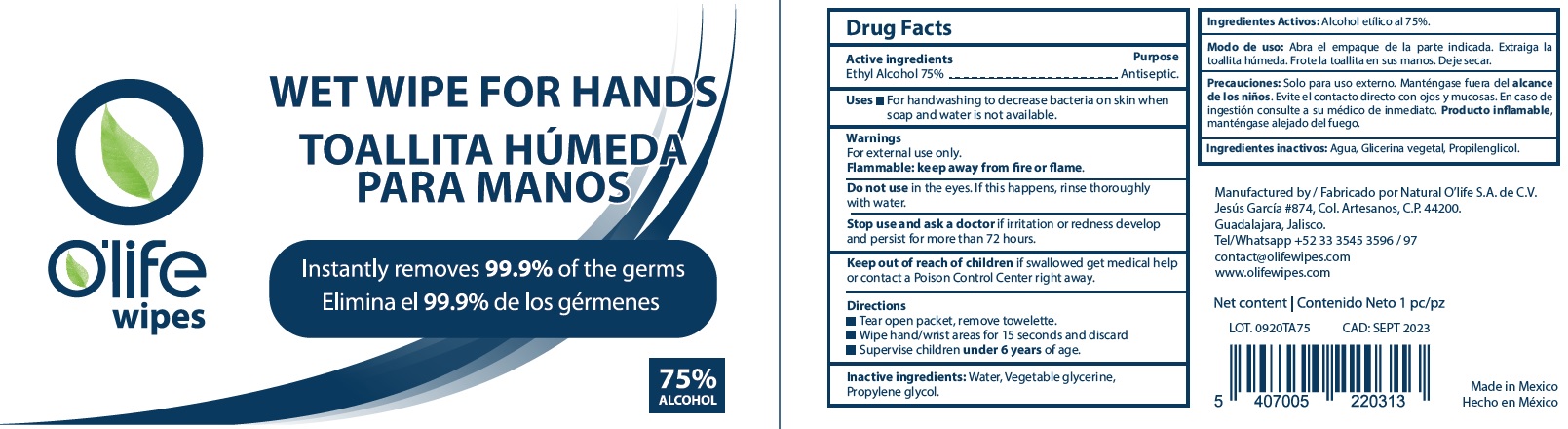 DRUG LABEL: Olife Wet Wipe for Hands
NDC: 80908-000 | Form: CLOTH
Manufacturer: Natural O'life, S.A. de C.V.
Category: otc | Type: HUMAN OTC DRUG LABEL
Date: 20201027

ACTIVE INGREDIENTS: ALCOHOL 0.75 mL/1 mL
INACTIVE INGREDIENTS: WATER; GLYCERIN; PROPYLENE GLYCOL

O’life Wet Wipe for Hands

Active ingredients

Ethyl Alcohol 75%

Purpose

Antiseptic.

Uses

- For handwashing to decrease bacteria on skin when soap and water is not available.

Warnings

For external use only.

Flammable: keep away from fire or flame.

Do not use

in the eyes. If this happens, rinse thoroughly with water.

Stop use and ask a doctor

if irritation or redness develop and persist for more than 72 hours.

Keep out of reach of children

if swallowed get medical help or contact a Poison Control Center right away.

Directions

- Tear open packet, remove towelette.
- Wipe hand/wrist areas for 15 seconds and discard
- supervise children under 6 years of age.

Inactive ingredients:

Water, Vegetable glycerine, Propylene glycol.